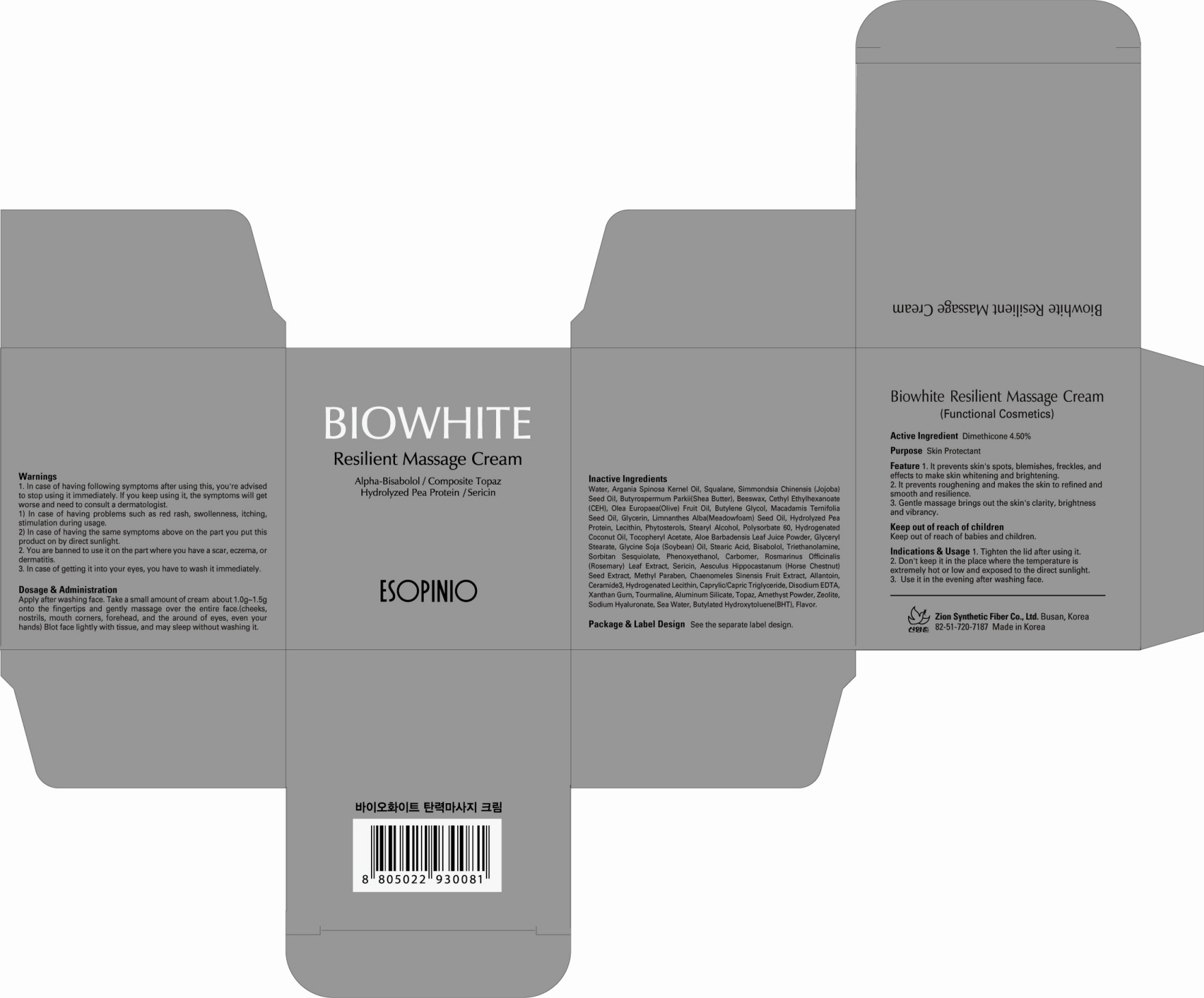 DRUG LABEL: BIOWHITE RESILIENT MASSAGE
NDC: 44781-210 | Form: CREAM
Manufacturer: ZION SYNTHETIC FIBER CO., LTD.
Category: otc | Type: HUMAN OTC DRUG LABEL
Date: 20120111

ACTIVE INGREDIENTS: DIMETHICONE 4.27 g/95 g
INACTIVE INGREDIENTS: WATER; ARGAN OIL; SQUALANE; JOJOBA OIL; SHEA BUTTER; YELLOW WAX; OLIVE OIL; BUTYLENE GLYCOL; GLYCERIN; MEADOWFOAM SEED OIL; LECITHIN, SOYBEAN; STEARYL ALCOHOL; POLYSORBATE 60; HYDROGENATED COCONUT OIL; ALOE VERA LEAF; GLYCERYL MONOSTEARATE; SOYBEAN OIL; STEARIC ACID

Drug Facts

Active ingredient: DIMETHICONE 4.50%

Inactive ingredients:
Water, Argania Spinosa Kernel Oil, Squalane, Simmondsia Chinensis (Jojoba) Seed Oil, Butyrospermum Parkii(Shea Butter), Beeswax, Cethyl Ethylhexanoate (CEH), Olea Europaea (Olive) Fruit Oil, Butylene Glycol, Macadamis Ternifolia Seed Oil, Glycerin, Limnanthes Alba (Meadowfoam) Seed Oil, Hydrolyzed Pea Protein, Lecithin, Phytosterols, Stearyl Alcohol, Polysorbate 60, Hydrogenated Coconut Oil, Tocopheryl Acetate, Aloe Barbadensis Leaf Juice Powder, Glyceryl Stearate, Glycine Soja (Soybean) Oil, Stearic Acid, Bisabolol, Triethanolamine, Sorbitan Sesquiolate, Phenoxyethanol, Carbomer, Rosmarinus Officinalis (Rosemary) Leaf Extract, Sericin, Aesculus Hippocastanum (Horse Chestnut) Seed Extract, Methyl Paraben, Chaenomeles Sinensis Fruit Extract, Allantoin, Ceramide3, Hydrogenated Lecithin, Caprylic/Capric Triglyceride, Disodium EDTA, Xanthan Gum, Tourmaline, Aluminum Silicate, Topaz, Amethyst Powder, Zeolite, Sodium Hyaluronate, Sea Water, Butylated Hydroxytoluene(BHT), Flavor

Purpose: Skin Protectant

Warnings:
In case of having following symptoms after using this, you're advised to stop using it immediately.
If you keep using it, the symptoms will get worse and need to consult a dermatologist.
- In case of having problems such as red rash, swollenness, itching, stimulation during usage.
- In case of having the same symptoms above on the part you put this product on by direct sunlight.
You are banned to use it on the part where you have a scar, eczema, or dermatitis.
In case of getting it into your eyes, you have to wash it immediately.

Keep out of reach of children:
Keep out of reach of babies and children.

Indications and usage:
Tighten the lid after using it.
Don't keep it in the place where the temperature is extremely hot or low and exposed to the direct sunlight.
Use it in the evening after washing face.

Dosage and administration:
Apply after washing face.
Take a small amount of cream about 1.0g-1.5g onto the fingertips and gently massage over the entire face.(cheeks, nostrils, mouth corners, forehead, and the around of eyes, even your hands)
Blot face lightly with tissue, and may sleep without washing it.